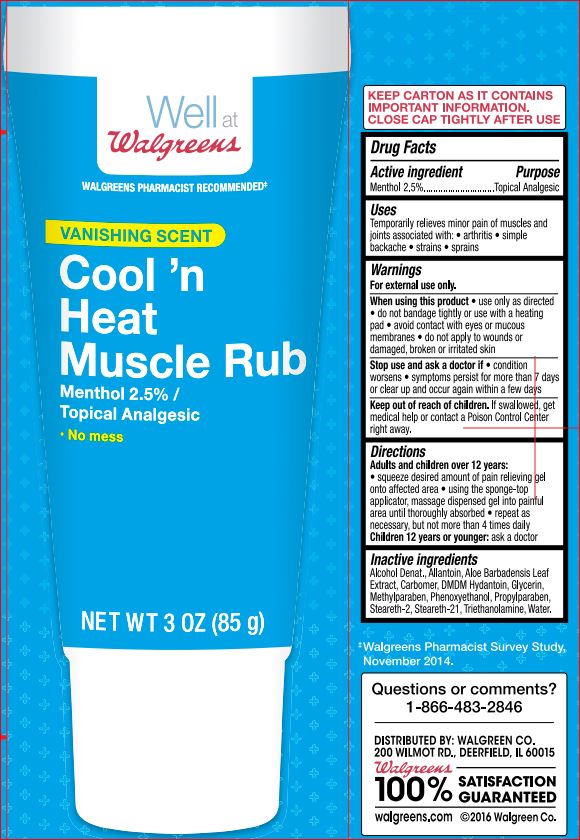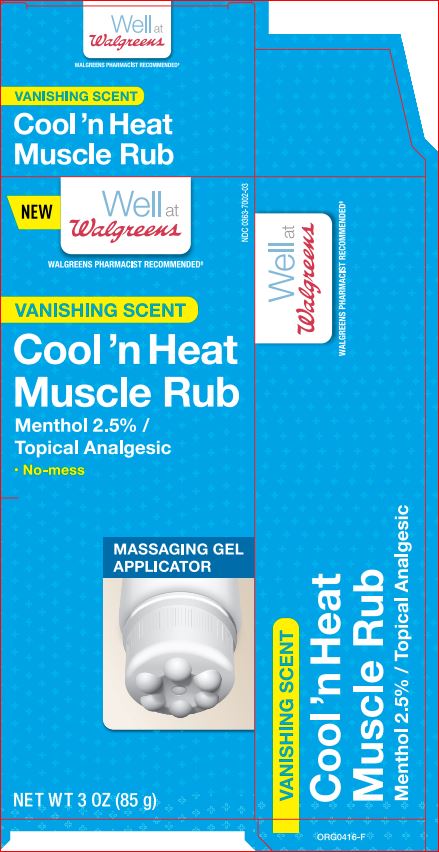 DRUG LABEL: Cooln Heat Muscle Rub
NDC: 0363-7002 | Form: GEL
Manufacturer: Walgreens
Category: otc | Type: HUMAN OTC DRUG LABEL
Date: 20180220

ACTIVE INGREDIENTS: Menthol 2.5 g/100 mL
INACTIVE INGREDIENTS: Alcohol; Allantoin; ALOE VERA LEAF; DMDM Hydantoin; Glycerin; Methylparaben; Phenoxyethanol; Propylparaben; Steareth-2; Steareth-21; TROLAMINE; WATER

Drug Facts

Active ingredient Purpose

Menthol 2.5% Topical Analgesic

Uses

temporarily reliefs minor pain associated with • arthritis • simple backache •strains • bruises

Warnings For external use only

When using this product

- use only as directed
- do not bandage tightly or use use with heating pad
- avoid contact with eyes or mucous membranes
- do not apply to wounds or damaged, broken or irritated skin

Directions

Adults and childern over 12 years:

- squeeze desired amount of pain relieving gel into painful area until throughly absorbed
- repeat as necessary, but not more than 4 times daily

Children 12 years or younger: ask a doctor

Inaction ingredients

Alcohol Denat.
Allantoin
Aloe Barbadensis Leaf Extract
Carbomer
DMDM Hydantoin
Glycerin
Methylparaben
Phenoxyethanol
Propylparaben
Steareth-2
Steareth-21
Triethanolamine
Water